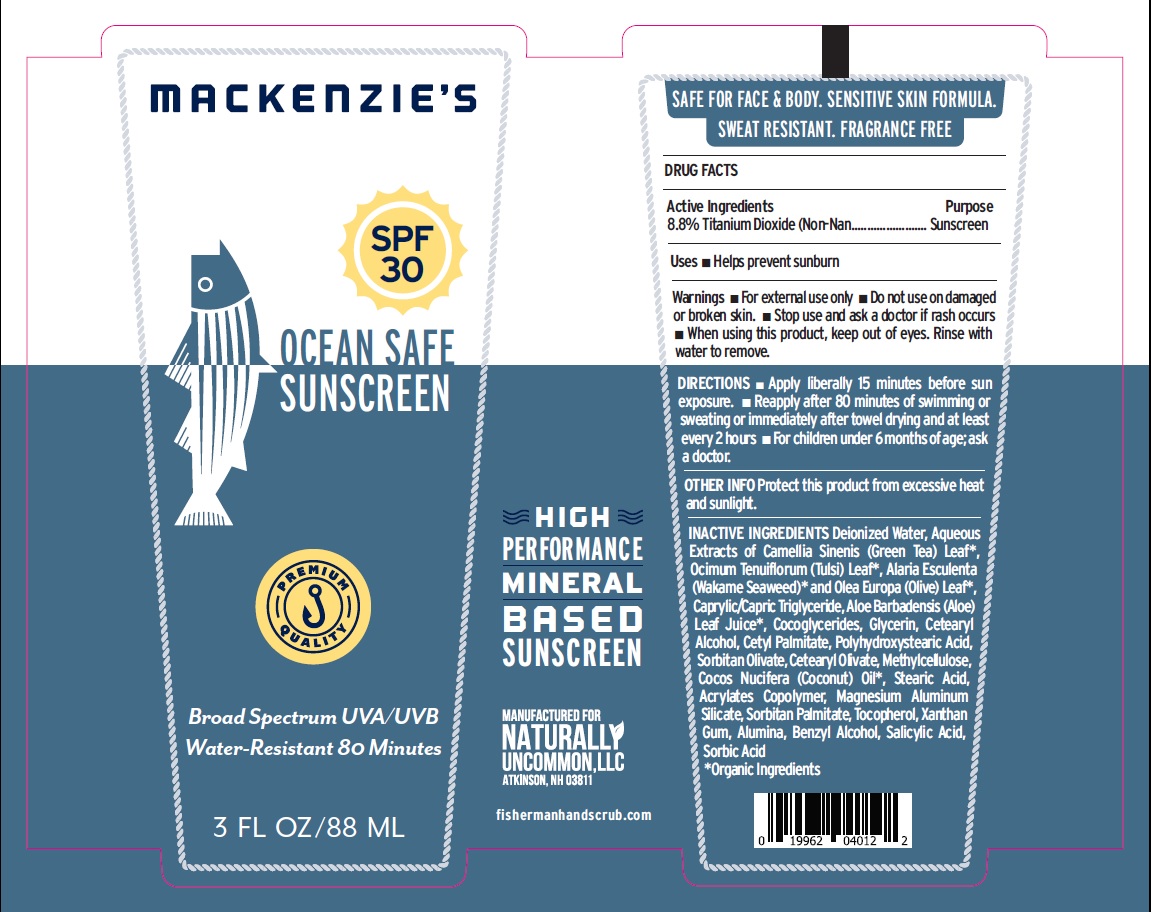 DRUG LABEL: OCEAN SAFE SUNSCREEN
NDC: 80325-003 | Form: CREAM
Manufacturer: Naturally Uncommon, LLC
Category: otc | Type: HUMAN OTC DRUG LABEL
Date: 20220623

ACTIVE INGREDIENTS: TITANIUM DIOXIDE 88 mg/88 mL
INACTIVE INGREDIENTS: WATER; GREEN TEA LEAF; HOLY BASIL LEAF; ALARIA ESCULENTA; OLEA EUROPAEA LEAF; ALOE; TRICAPRIN; COCO-GLYCERIDES; GLYCERIN; CETOSTEARYL ALCOHOL; CETYL PALMITATE; POLYHYDROXYSTEARIC ACID STEARATE; SORBITAN OLIVATE; CETEARYL OLIVATE; METHYLCELLULOSE, UNSPECIFIED; COCONUT OIL; STEARIC ACID; LUVISET 360; MAGNESIUM ALUMINUM SILICATE; SORBITAN MONOPALMITATE; TOCOPHEROL; XANTHAN GUM; ALUMINUM OXIDE; BENZYL ALCOHOL; SALICYLIC ACID; SORBIC ACID

OCEAN SAFE SUNSCREEN
Broad Spectrum UVA/UVB Water-Resistant 80 Minutes
SAFE FOR FACE & BODY
SENSITIVE SKIN FORMULA
SWEAT RESISTANT
FRAGRANCE FREE
HIGH PERFORMANCE MINERAL BASED SUNSCREEN
3 FL OZ/ 88 ML

DRUG FACTS Active Ingredients

8.8% Titanium Dioxide

Purpose

(Non-Nano)...........Sunscreen

Uses

■ Helps prevent sunburn.

Warnings

■ For external use only.
■ Do not use on damaged or broken skin.
■ Stop use and ask a doctor if rash occurs.
■ When using this product, keep out of eyes. Rinse with water to remove.

DIRECTIONS

■ Apply liberally 15 minutes before sun exposure.
■ Reapply after 80 minutes of swimming or sweating or immediately after towel drying and at least every 2 hours.
■ For children under 6 months of age; ask a doctor.

OTHER INFO

Protect this product from excessive heat and sunlight.

INACTIVE INGREDIENTS

Deionized Water, Aqueous Extracts of Camellia Sinenis (Green Tea) Leaf*, Ocimum Tenuiflorum (Tulsi) Leaf*, Alaria Esculenta (Wakame Seaweed)*, Olea Europa (Olive) Leaf*, Caprylic/Capric Triglyceride, Aloe Barbadensis (Aloe) Leaf Juice*, Cocoglycerides, Glycerin, Cetearyl Alcohol, Cetyl Palmitate, Polyhydroxystearic Acid, Sorbitan Olivate, Cetearyl Olivate, Methylcellulose, Cocos Nucifera (Coconut) Oil*, Stearic Acid, Acrylates Copolymer, Magnesium Aluminum Silicate, Sorbitan Palmitate, Tocopherol, Xanthan Gum, Alumina, Benzyl Alcohol, Salicylic Acid and Sorbic Acid.
*Organic Ingredients.

MANUFACTURED FOR
NATURALLY UNCOMMON, LLC
ATKINSON, NH03811
fishermanhandscrub.com

PACKAGE LABEL.PRINCIPAL DISPLAY PANEL

OCEAN SAFE SUNSCREEN-88 ML - NDC-80325-003-01- TUBE LABEL.